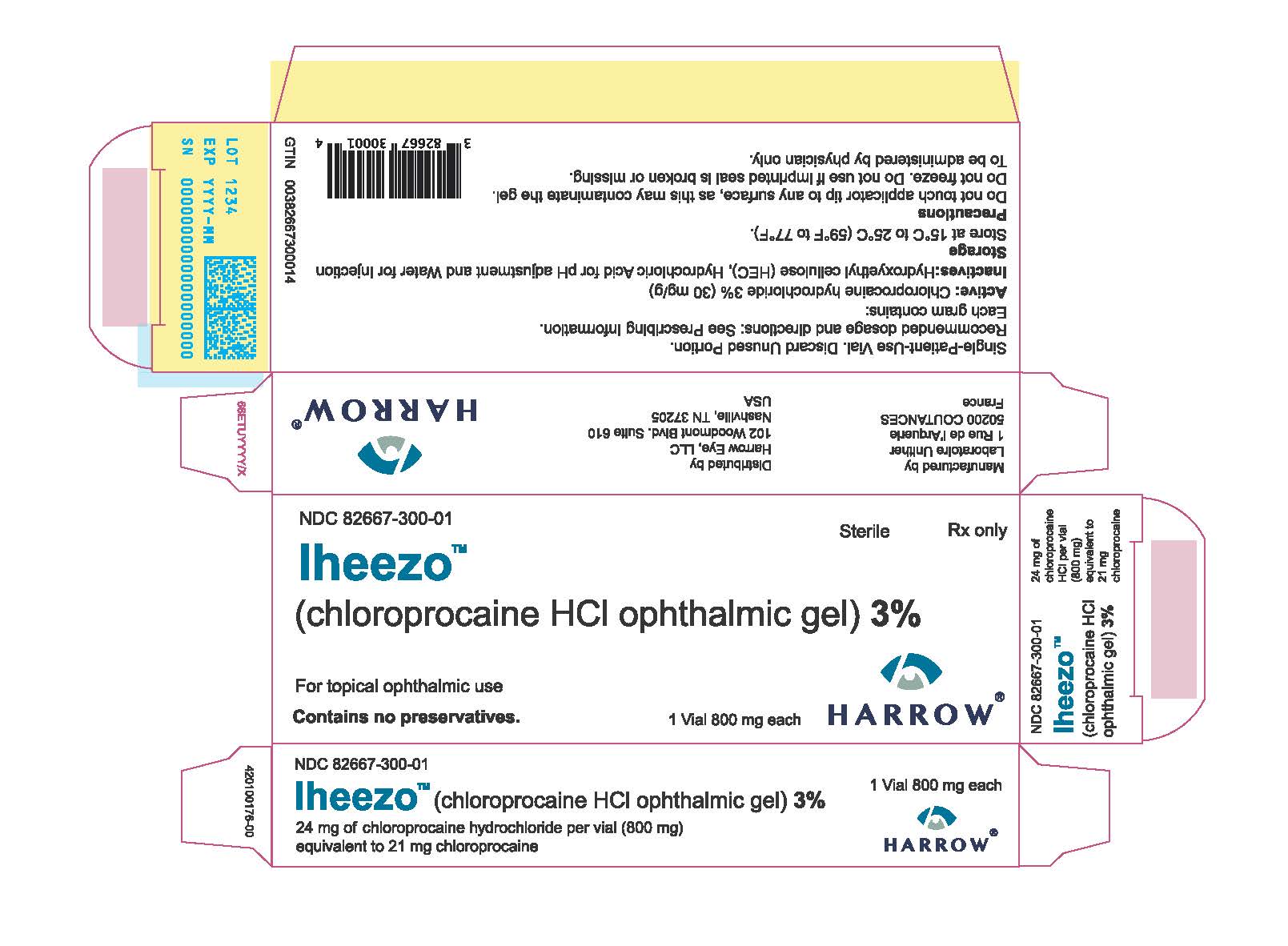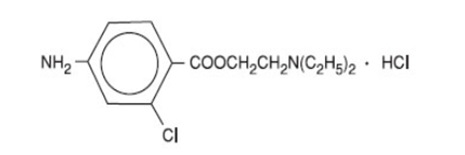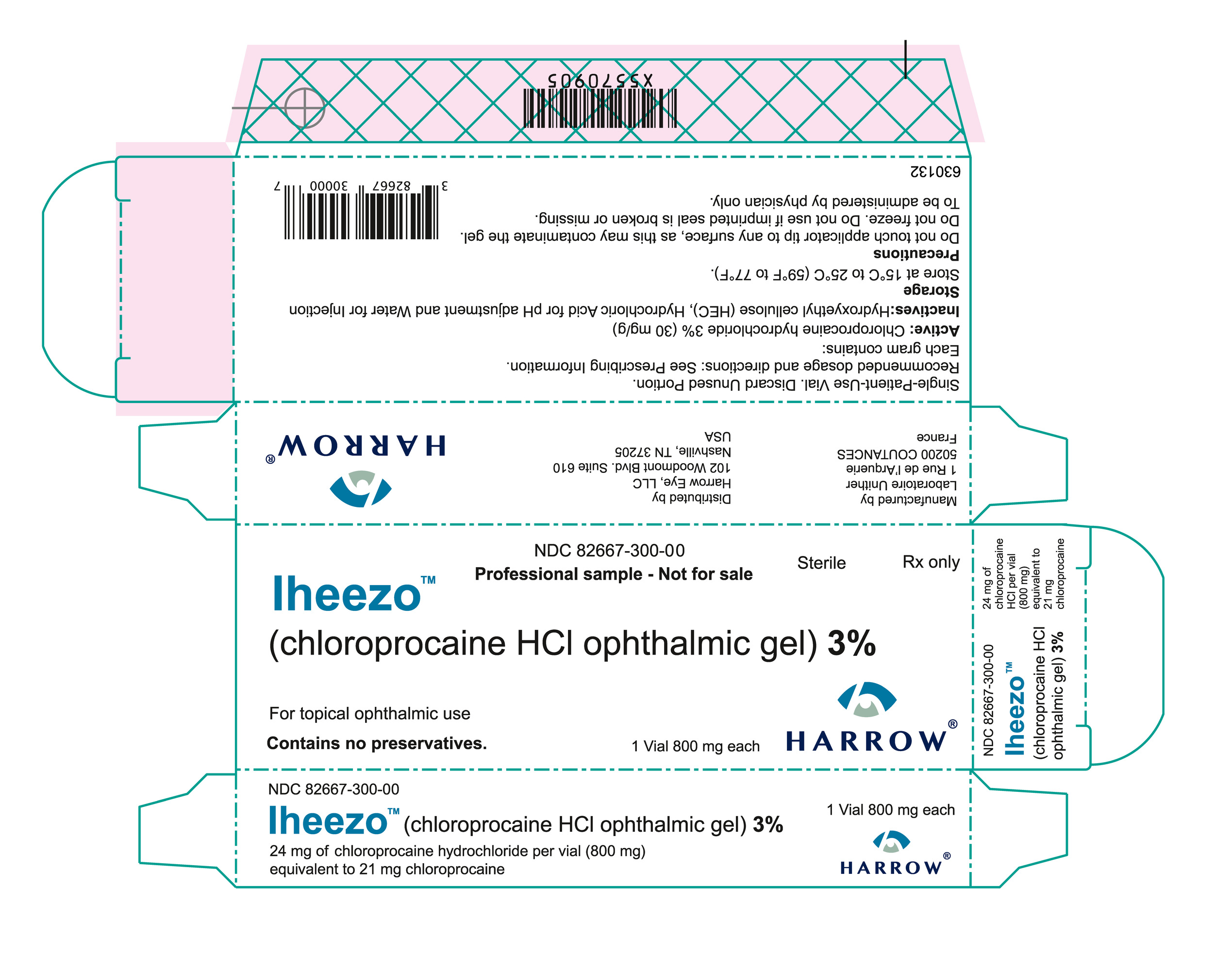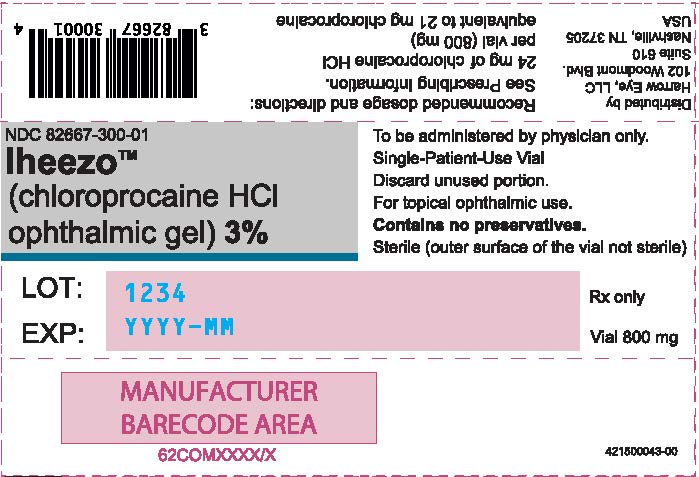 DRUG LABEL: IHEEZO
NDC: 82667-300 | Form: GEL
Manufacturer: Harrow Eye, LLC
Category: prescription | Type: HUMAN PRESCRIPTION DRUG LABEL
Date: 20251031

ACTIVE INGREDIENTS: CHLOROPROCAINE HYDROCHLORIDE 24 mg/800 mg
INACTIVE INGREDIENTS: HYDROXYETHYL CELLULOSE, UNSPECIFIED; WATER; HYDROCHLORIC ACID

HIGHLIGHTS OF PRESCRIBING INFORMATION

These highlights do not include all the information needed to use IHEEZOTMsafely and effectively. See full prescribing information for IHEEZOTM.
IHEEZOTM(chloroprocaine hydrochloride ophthalmic gel) 3%, for topical ophthalmic use
Initial U.S. Approval: 1955

1 INDICATIONS AND USAGE

IHEEZOTMis an ester anesthetic indicated for ocular surface anesthesia. (1)

2 DOSAGE AND ADMINISTRATION

- The recommended dose of IHEEZOTMis 3 drops applied topically to the ocular surface in the area of the planned procedure. (2)
- IHEEZOTMmay be reapplied as needed to maintain anesthetic effect. (2)

3 DOSAGE FORMS AND STRENGTHS

IHEEZOTM(chloroprocaine hydrochloride ophthalmic gel) 3% contains 24 mg of chloroprocaine hydrochloride per vial (800 mg). Clear, colorless to light yellow gel in single‑patient‑use vial. (3)

4 CONTRAINDICATIONS

IHEEZOTMis contraindicated in patients with a history of hypersensitivity to any component of this preparation. (4)

5 WARNINGS AND PRECAUTIONS

- Not for Injection or Intraocular Administration (5.1).
- Corneal Injury Due to Insensitivity (5.2).
- Corneal Opacification (5.3)
- For Administration by Healthcare Provider: IHEEZOTMis not intended for patient self-administration (5.5).

6 ADVERSE REACTIONS

Most common adverse reaction is mydriasis (approximately 25%) (6.1)

To report SUSPECTED ADVERSE REACTIONS, contact Harrow at 844.446.6979 or FDA at 1-800-FDA-1088 orwww.fda.gov/medwatch.

FULL PRESCRIBING INFORMATION

1 INDICATIONS AND USAGE

IHEEZOTMis indicated for ocular surface anesthesia.

2 DOSAGE AND ADMINISTRATION

The recommended dose of IHEEZOTMis 3 drops applied topically to the ocular surface in the area of the planned procedure. IHEEZOTMmay be reapplied as needed to maintain anesthetic effect.

3 DOSAGE FORMS AND STRENGTHS

IHEEZOTM(chloroprocaine hydrochloride ophthalmic gel) 3% contains 24 mg of chloroprocaine hydrochloride per vial (800 mg of gel).

4 CONTRAINDICATIONS

IHEEZOTMis contraindicated in patients with a history of hypersensitivity to any component of this preparation.

5 WARNINGS AND PRECAUTIONS

5.1 Not for Injection or Intraocular Administration

IHEEZOTMshould not be injected or intraocularly administered.

5.2 Corneal Injury Due to Insensitivity

Patients should not touch the eye for at least 10 to 20 minutes after using anesthetic as accidental injuries can occur due to insensitivity of the eye.

5.3 Corneal Opacification

Prolonged use of a topical ocular anesthetic may produce permanent corneal opacification and ulceration with accompanying visual loss.

5.4 Risk of Contamination

Do not touch the dropper tip to any surface as this may contaminate the gel.

5.5 For Administration by Healthcare Provider

IHEEZOTMis indicated for administration under the direct supervision of a healthcare provider. IHEEZOTMis not intended for patient self-administration.

6 ADVERSE REACTIONS

6.1 Clinical Trials Experience

Because clinical trials are conducted under widely varying conditions, adverse reaction rates observed in the clinical trials of a drug cannot be directly compared to rates in the clinical trials of another drug and may not reflect the rates observed in practice.

The data described below reflect 201 patients undergoing various surgical ocular procedures in two placebo-controlled trials (Study 1 and Study 2). Patients in Study 1 were randomized to receive a single instillation of 3 drops of IHEEZOTMor placebo. Patients in Study 2 were randomized to receive a single or multiple instillations of 1, 3 or 3+3 drops of IHEEZOTMor placebo.

The most common adverse reactions in these studies, (incidence greater than or equal to 5%) following IHEEZOTMadministration were mydriasis, conjunctival hyperemia and eye irritation.

Adverse Reactions Reported in Controlled Trials

Table 1. Adverse Reactions in 5% or more of IHEEZOTMTreated Patients in Studies 1 and 2

 | IHEEZOTM | Placebo
Preferred Term | N=151; n (%) | N=50; n (%)
Mydriasis | 39 (26%) | 1 (2%)
Conjunctival hyperemia | 16 (11%) | 6 (12%)
Eye irritation | 9 (6%) | 2 (4%)

8 USE IN SPECIFIC POPULATIONS

8.1 Pregnancy

Risk Summary

There are no adequate and well-controlled studies of IHEEZOTMuse in pregnant women to inform a drug associated risk. There are no animal reproduction studies for chloroprocaine.

8.2 Lactation

Risk Summary

There are no data on the presence of chloroprocaine in human milk, the effects on the breastfed infant, or the effects on milk production. The developmental and health benefits of breastfeeding should be considered along with the mother’s clinical need for IHEEZOTMand any potential adverse effects on the breastfed infant from IHEEZOTM.

8.4 Pediatric Use

The safety and effectiveness of IHEEZOTMhave not been established in pediatric patients.

8.5 Geriatric Use

No overall differences in safety or effectiveness of IHEEZOTMhave been observed between elderly and younger patients.

11 DESCRIPTION

IHEEZOTMis a sterile, single-patient‑use ophthalmic gel preparation for topical ocular anesthesia containing chloroprocaine hydrochloride as the active pharmaceutical ingredient. Chloroprocaine hydrochloride is an ester anesthetic. It is a water-soluble white crystalline powder and its chemical name is 2-(Diethylamino)ethyl 4‑amino-2-chlorobenzoate monohydrochloride. The molecular weight is 307.22 and the molecular formula is C13H19ClN2O2·HCl. It is represented by the following structural formula:

IHEEZOTMcontains:

Active: 30 mg of chloroprocaine hydrochloride (equivalent to 26 mg of chloroprocaine) per gram of gel.

Inactive ingredients: Hydroxyethyl Cellulose (HEC), and Water for Injection. The pH may be adjusted to 3.0 to 5.0 with Hydrochloric Acid. This product does not contain an antimicrobial preservative.

12 CLINICAL PHARMACOLOGY

12.1 Mechanism of Action

Chloroprocaine, like other local anesthetics, blocks the generation and the conduction of nerve impulses, presumably by increasing the threshold for electrical excitation in the nerve, by slowing the propagation of the nerve impulse, and by reducing the rate of rise of the action potential. In general, the progression of anesthesia is related to the diameter, myelination, and conduction velocity of affected nerve fibers. Clinically, the order of loss of nerve function is as follows: (1) pain, (2) temperature, (3) touch, (4) proprioception, and (5) skeletal muscle tone.

12.3 Pharmacokinetics

The systemic exposure to chloroprocaine following topical ocular administration of IHEEZOTMhas not been studied.

Elimination

Metabolism

Chloroprocaine is metabolized by plasma pseudocholinesterases and nonspecific esterases in ocular tissues. Chloroprocaine is rapidly metabolized in plasma by hydrolysis of the ester linkage by pseudocholinesterase. The hydrolysis of chloroprocaine results in the production of ß-diethylaminoethanol and 2-chloro-4-aminobenzoic acid, which inhibits the action of the sulfonamides.

Excretion

Chloroprocaine plasma half-life in vitro is approximately 25 seconds in adults and approximately 43 seconds in neonates. The kidney is the main excretory organ for most local anesthetics and their metabolites. Urinary excretion is affected by urinary perfusion and factors affecting urinary pH.

13 NONCLINICAL TOXICOLOGY

13.1 Carcinogenesis, Mutagenesis, Impairment of Fertility

Carcinogenesis

Long-term studies in animals to evaluate carcinogenic potential of chloroprocaine have not been conducted.

Mutagenesis

2-chloroprocaine and the main metabolite, ACBA, were negative in the in vitro bacterial reverse mutation test (Ames assay) and the in vitro chromosome aberrations assay.

Impairment of Fertility

Studies in animals to evaluate the impairment of fertility have not been conducted with chloroprocaine.

14 CLINICAL STUDIES

14.1 Study 1 and 2

Study 1(NCT04779606) and Study 2(NCT04753710) were randomized, double-blinded placebo-controlled studies conducted to evaluate the efficacy, safety, and local tolerability of IHEEZOTMin 145 healthy volunteers.

In Study 1, 85 healthy male and female were randomized in a 4:1 ratio to receive a single ocular instillation of IHEEZOTM(N=68) or placebo (N=17). The double blinded treatment included a IHEEZOTMor a placebo dose of 3 drops instilled at 1 minute ± 15 seconds intervals in the right eye of each volunteer. The median age was 39 years (range 19 to 55 years); 59% female and 41% male.

In Study 2, 60 healthy male and female were randomized (40:20) to receive single or multiple ocular instillations of IHEEZOTMdose of 3 drops in the right eye. The median age was 25 years (range 18 to 59 years); 54% female ad 46% male.

The efficacy in Study 1 and 2 was determined by proportion of patients achieving full conjunctival anesthesia evaluated by conjunctival pinching, 5 minutes after administration.

Efficacy results of Study 1

The proportion of subjects with successful anesthesia was 90% in IHEEZOTMgroup and 12% in the placebo group (p<0.01). The median time for the IHEEZOTMgroup achieving anesthesia was 0.67 minutes. The median duration of anesthesia was 14.3 minutes.

Efficacy results of Study 2

The proportion of subjects with successful anesthesia was 95% in the IHEEZOTMgroup and 20% in the placebo group (p<0.01). The median time for the IHEEZOTMgroup achieving anesthesia was 0.67 minutes. The median duration of anesthesia was 19.3 minutes.

14.2 Study 3

Study 3(NCT04685538) was a randomized, prospective, multi-center, active-controlled, observer-masked study conducted to evaluate the efficacy and safety of IHEEZOTM(N=166) versus tetracaine ophthalmic solution 0.5% (N=172) in patients undergoing cataract surgery.

The primary endpoint was defined as the proportion of patients in each treatment group gaining successful anesthesia without any supplementation. On average, patients needed 1-1.5 minutes to obtain sufficient anesthesia to successfully perform the surgical procedure which lasted on average 22 minutes.

No patient treated with IHEEZOTMrequired supplemental treatment to complete the intended surgical procedure.

16 HOW SUPPLIED/STORAGE AND HANDLING

IHEEZOTM(chloroprocaine hydrochloride ophthalmic gel) 3% is supplied as a sterile, clear, colorless to light yellow gel in a single-patient‑use vial. Each single‑patient‑use vial contains 24 mg chloroprocaine in 800 mg of gel.

Aluminum pouch containing 1 LDPE single-patient‑use vial of IHEEZOTM.

The outer surface of the vial is not sterile.

NDC 82667-300-01 Package of 1 unit of 1.25 mL single-patient‑use vial (800 mg filled)

NDC 82667-300-10 Package of 10 units of 1.25 mL single-patient‑use vials (800 mg filled)

NDC 82667-300-00 Sample package of 1 unit of 1.25 mL single-patient-use vial (800 mg filled)

Storage

Store at 15°C to 25°C (59°F to 77°F).

Discard after use.

17 PATIENT COUNSELING INFORMATION

Eye Care Precaution

Do not touch the dropper tip to any surface as this may contaminate the gel.

Advise patients that their eyes will be insensitive for up to 20 minutes due to the effect of the anesthetic, and that care should be taken to avoid accidental injuries.

Manufactured by

Laboratoire Unither

1 Rue de l’Arquerie

50200 COUTANCES

France

Distributed by

Harrow Eye, LLC

102 Woodmont Blvd. Suite 610

Nashville, TN 37205

USA

PRINCIPAL DISPLAY PANEL - Carton

NDC 82667-300-01 Sterile Rx Only

IheezoTM

(chloroprocaine hydrochloride ophthalmic gel) 3%

For topical ophthalmic use

Contains no preservatives. 1 Vial 800 mg each HARROW®

PRINCIPAL DISPLAY PANEL - Pouch

NDC 82667-300-01

IheezoTM

(chloroprocaine hydrochloride ophthalmic gel) 3%

To be administered by physician only.

Single-Patient-Use Vial

Discard unused portion.

For topical ophthalmic use.

Contains no preservatives.

Sterile (outer surface of the vial not sterile)

LOT: 1234

EXP: YYYY-MM

Rx Only

Vial 800 mg

PRINCIPAL DISPLAY PANEL - Sample Carton

NDC 82667-300-00

Professional sample - Not for sale Sterile Rx Only

IheezoTM

(chloroprocaine hydrochloride ophthalmic gel) 3%

For topical ophthalmic use

Contains no preservatives. 1 Vial 800 mg each HARROW®